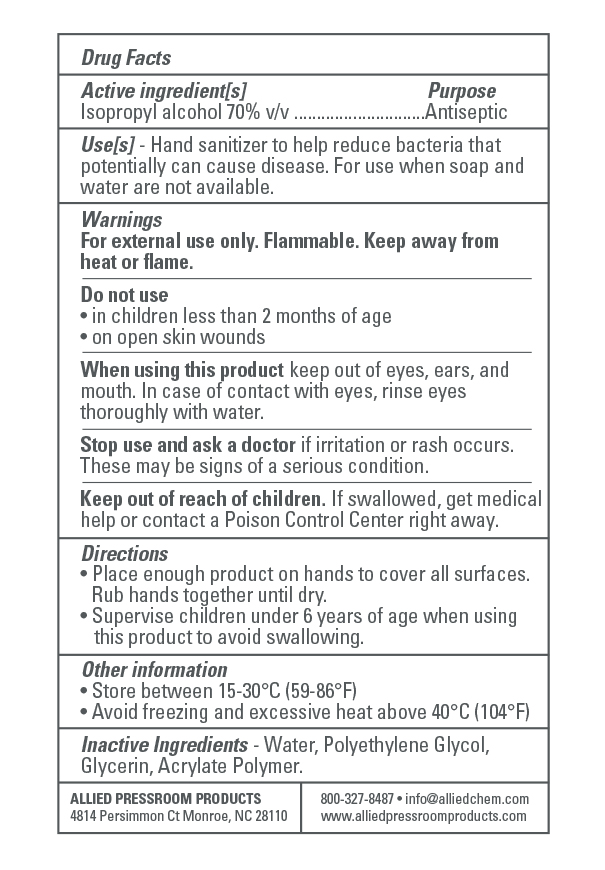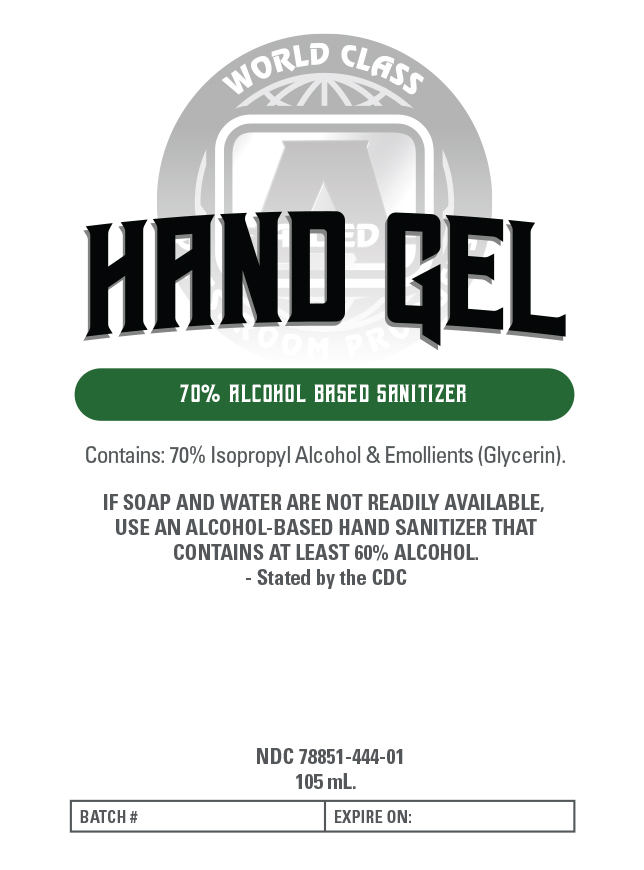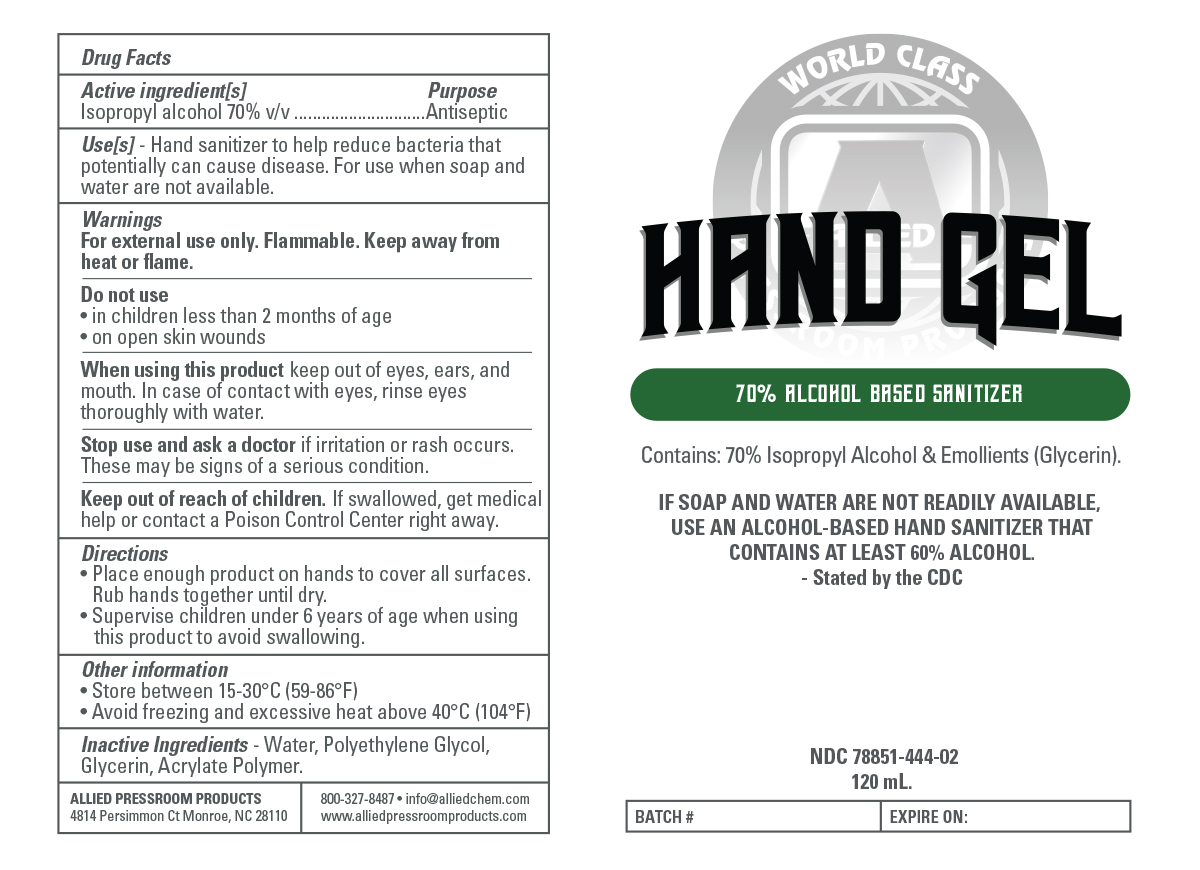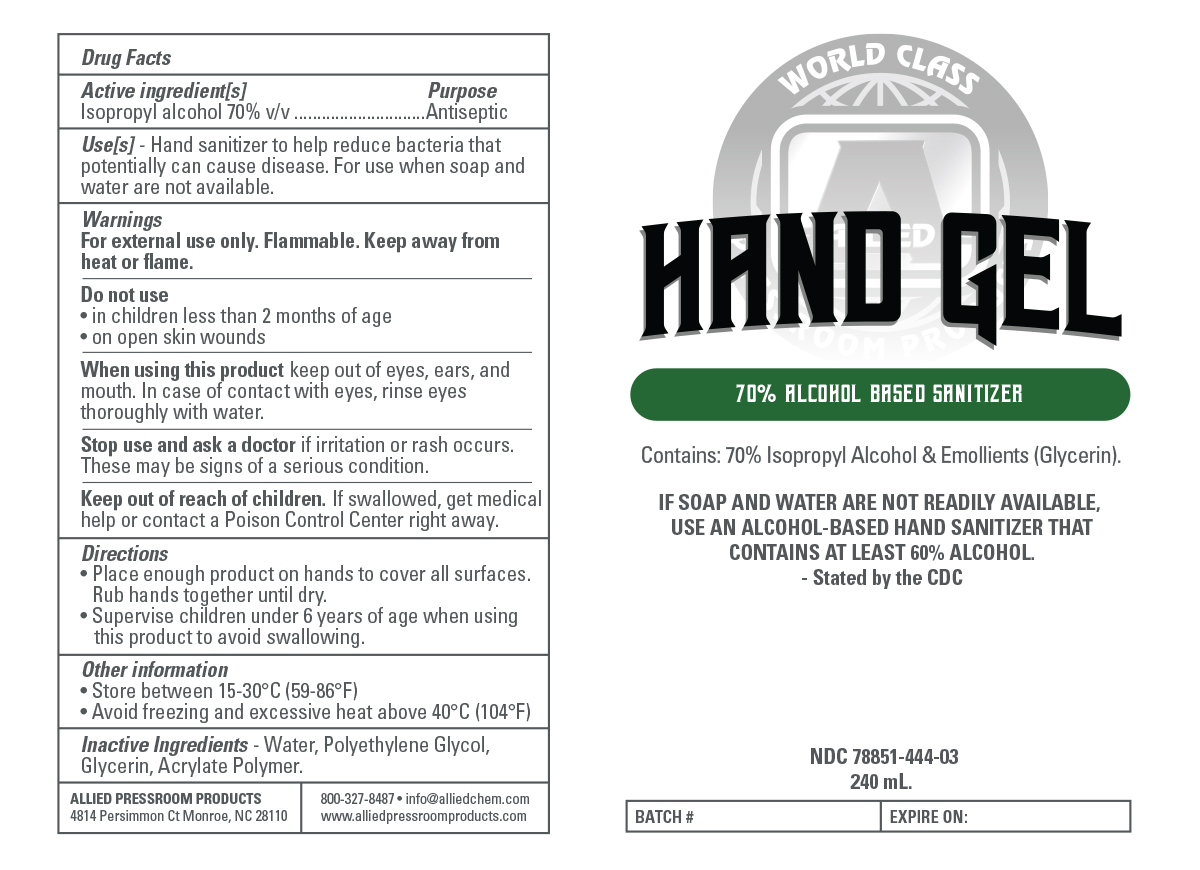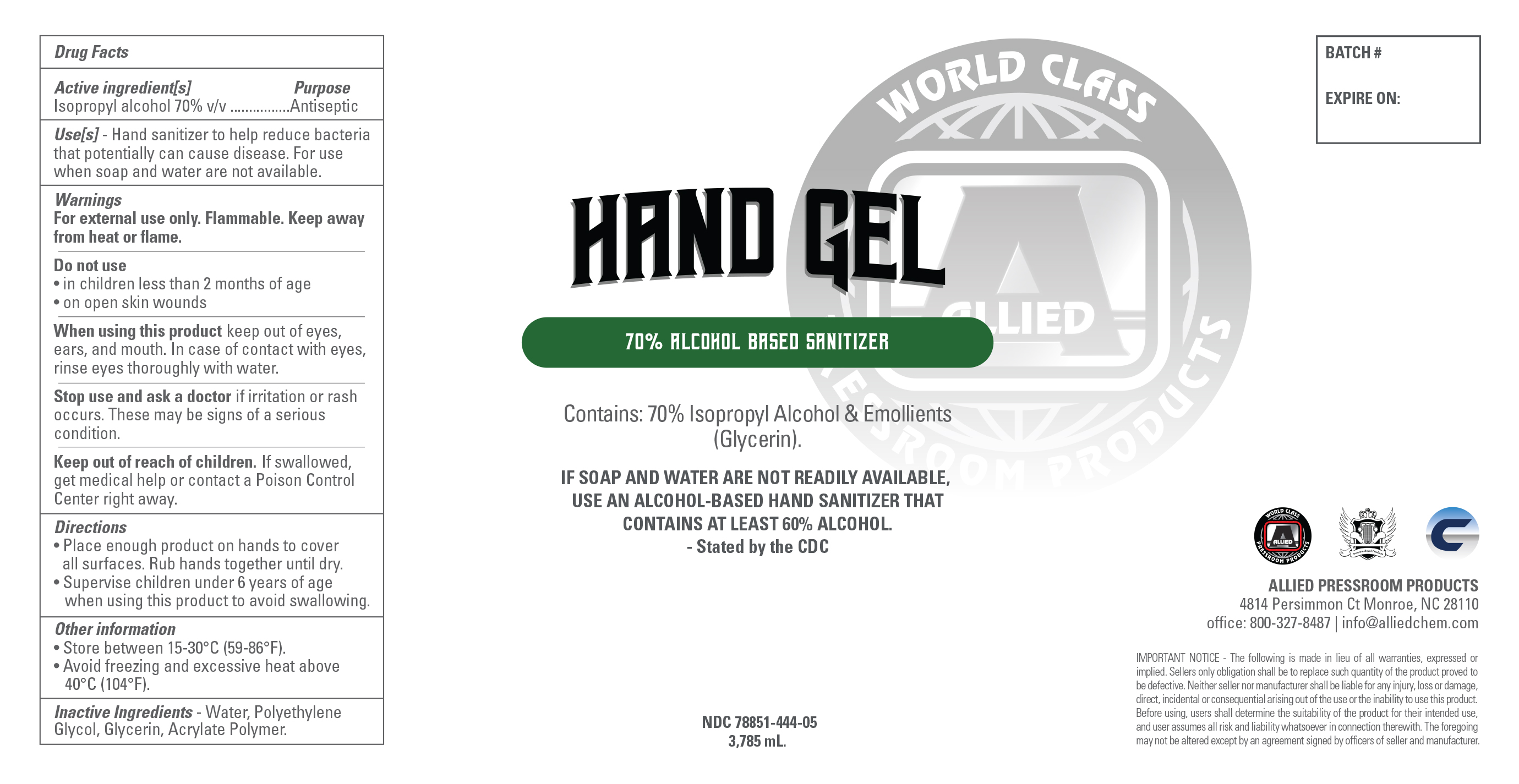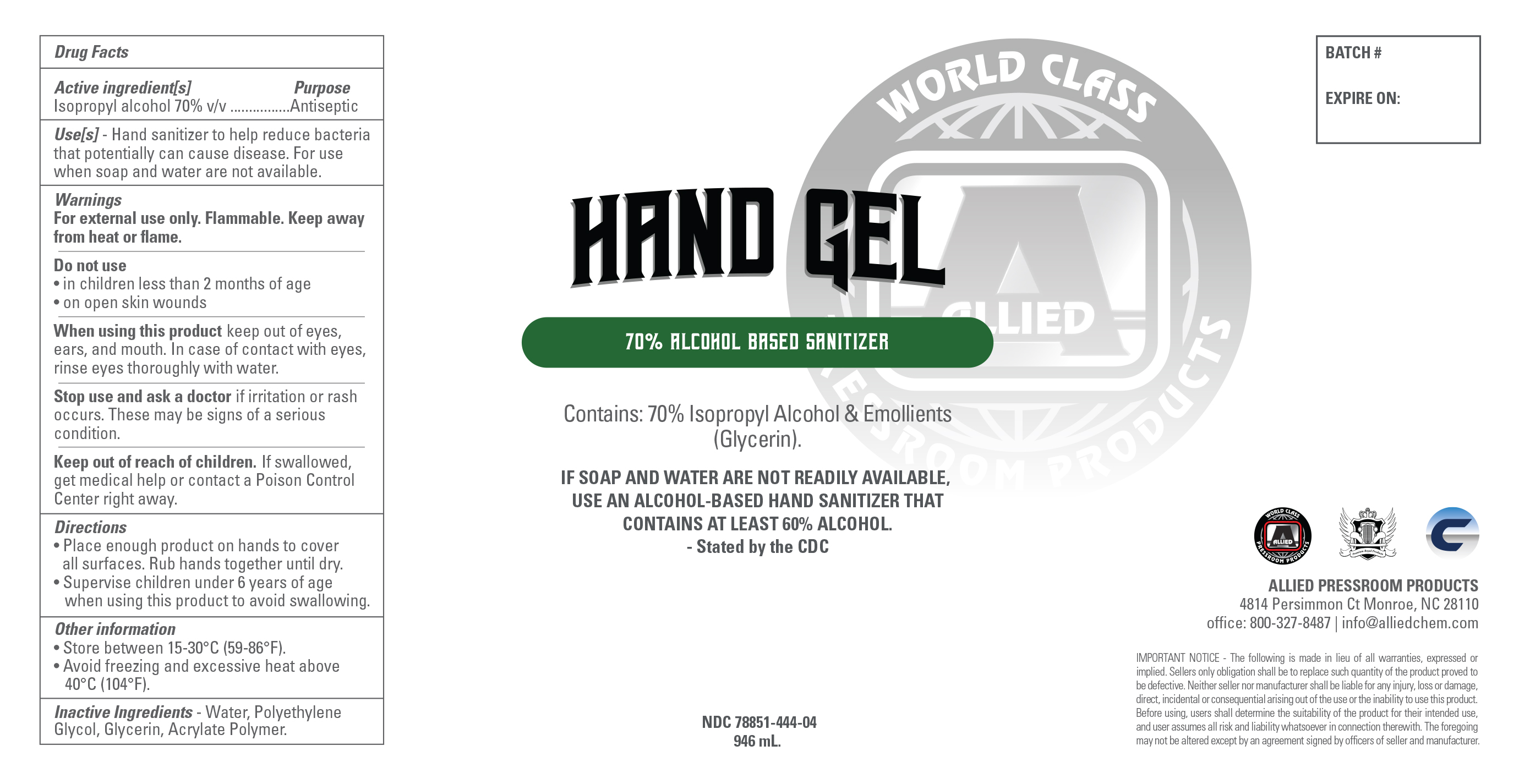 DRUG LABEL: Hand Gel Sanitizer
NDC: 78851-444 | Form: GEL
Manufacturer: Allied Pressroom Products
Category: otc | Type: HUMAN OTC DRUG LABEL
Date: 20200623

ACTIVE INGREDIENTS: ISOPROPYL ALCOHOL 70 mL/100 mL
INACTIVE INGREDIENTS: WATER; POLYETHYLENE GLYCOL 1000 1.2 mL/100 mL; ALLYL METHACRYLATE/GLYCOL DIMETHACRYLATE CROSSPOLYMER (LOW ALLYL METHACRYLATE) 0.3 mL/100 mL; GLYCERIN 1 mL/100 mL

Hand Gel Isopropyl Alcohol Sanitizer

This is an isopropyl alcohol based hand sanitizer manufactured following the CDC recomendation of using an alcohol concentration of more than 60 % v/v alcohol when soap and water is not available.

It is manufactured by gelling a 70 % isopropyl alcohol solution with the minimum of an acrylate polymer to create a clear gel that is easy to apply and does not evaporate as readiliy as the liquid versions to provide sufficient dwell time to be effective.

The hand sanitizer is manufactured using only the following United States Pharmacopoeia (USP) grade ingredients in the preparation of the product::

1. Alcohol (isopropyl alcohol) (USP or Food Chemical Codex (FCC) grade) (70%, volume/volume (v/v)) in an aqueous solution denatured according to Alcohol and Tobacco Tax and Trade Bureau regulations in 27 CFR part 20.
2. Glycerin (1.00 % v/v)..
3. Polypropylene Glycol (1.2 % v/v)..
4. Acrylate Polymer (0.3% v/v).
5. Sterile distilled water or boiled cold water.

No other materials are used.

Active Ingredient(s)

Isopropyl Alcohol 70% v/v. Purpose: Antiseptic

Purpose

Antiseptic, Hand Sanitizer

Use

Hand Sanitizer to help reduce bacteria that potentially can cause disease. For use when soap and water are not available.

Warnings

For external use only. Flammable. Keep away from heat or flame

Do not use

- in children less than 2 months of age
- on open skin wounds

When using this product keep out of eyes, ears, and mouth. In case of contact with eyes, rinse eyes thoroughly with water.
Stop use and ask a doctor if irritation or rash occurs. These may be signs of a serious condition.
Keep out of reach of children. If swallowed, get medical help or contact a Poison Control Center right away.

Stop use and ask a doctor if irritation or rash occurs. These may be signs of a serious condition.

Keep out of reach of children. If swallowed, get medical help or contact a Poison Control Center right away.

Directions

- Place enough product on hands to cover all surfaces. Rub hands together until dry.
- Supervise children under 6 years of age when using this product to avoid swallowing.

Other information

- Store between 15-30C (59-86F)
- Avoid freezing and excessive heat above 40C (104F)

Inactive ingredients

Water, Polypropylene Glycol, glycerin, Acrylate polymer.

Package Label - Principal Display Panel

3785 ml NDC 78851-444-05

946 ml NDC 78851-444-04

240 ml NDC 78851-444-03

120 ml MDC 78851-444-02

105 ml NDC 78851-444-01 back 105 105 ml NDC 78851-444-01 front